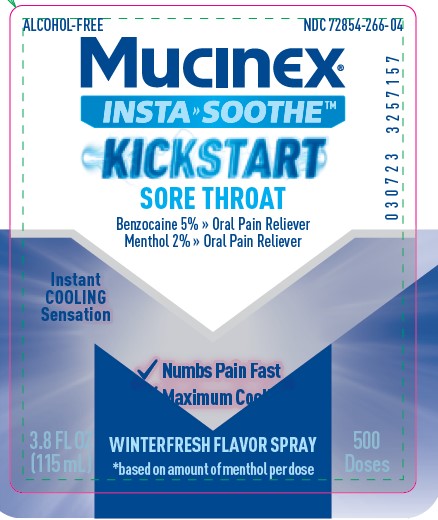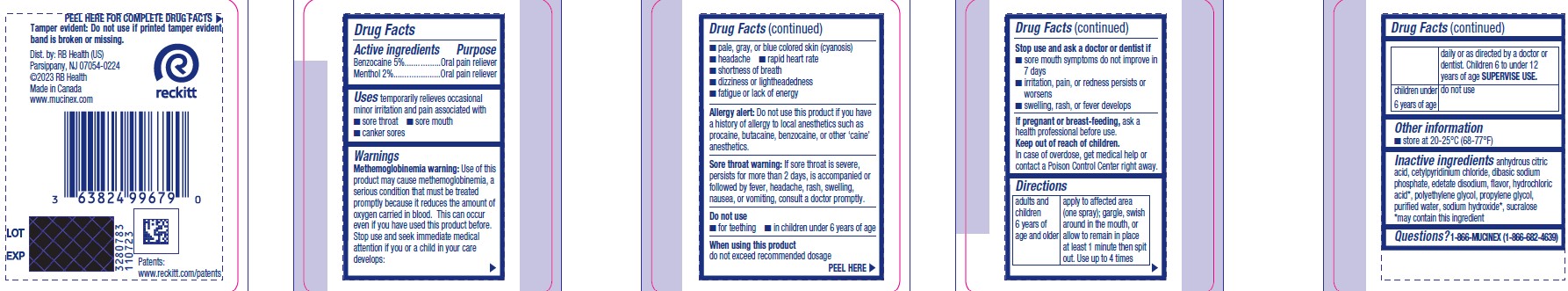 DRUG LABEL: Mucinex Insta soothe
NDC: 72854-266 | Form: SPRAY
Manufacturer: RB Health (US) LLC
Category: otc | Type: HUMAN OTC DRUG LABEL
Date: 20251223

ACTIVE INGREDIENTS: BENZOCAINE 5 g/100 mL; MENTHOL, UNSPECIFIED FORM 2 g/100 mL
INACTIVE INGREDIENTS: EDETATE DISODIUM; POLYETHYLENE GLYCOL, UNSPECIFIED; SODIUM PHOSPHATE, DIBASIC, UNSPECIFIED FORM; WATER; ANHYDROUS CITRIC ACID; SUCRALOSE; CETYLPYRIDINIUM CHLORIDE; HYDROCHLORIC ACID; PROPYLENE GLYCOL; SODIUM HYDROXIDE

Mucinex® INSTASOOTHE™ Sore Throat Winter Fresh

Active Ingredients

Benzocaine 5%

Menthol 2%

Purpose

Oral Pain Reliever

Uses

temporarily relieves occasional minor irritation and pain associated with
■ sore throat

■ sore mouth
■ canker sores

Warnings

Methemoglobinemia warning: Use of this product may cause methemoglobinemia, a serious condition that must be treated promptly because it reduces the amount of oxygen carried in blood. This can occur even if you have used this product before. Stop use and seek immediate medical attention if you or a child in your care develops:

■ pale, gray, or blue colored skin (cyanosis)
■ headache

■ rapid heart rate
■ shortness of breath
■ dizziness or lightheadedness
■ fatigue or lack of energy

Allergy alert: Do not use this product if you have a history of allergy to local anesthetics such as procaine, butacaine, benzocaine, or other ‘caine’ anesthetics.

Sore throat warning: If sore throat is severe, persists for more than 2 days, is accompanied or followed by fever, headache, rash, swelling, nausea, or vomiting, consult a doctor promptly.

Do not use
■ for teething

■ in children under 6 years of age

When using this product:
do not exceed recommended dosage

Stop use and ask a doctor or dentist if
■ sore mouth symptoms do not improve in 7 days
■ irritation, pain, or redness persists or worsens
■ swelling, rash, or fever develops

If pregnant or breast-feeding, ask a health professional before use.

Keep out of reach of children.

In case of overdose, get medical help or contact a Poison Control Center right away.

Directions

Adults and children 6 years of age and older:

- apply to affected area (one spray); gargle, swish around in the mouth, or allow to remain in place at least 1 minute then spit out. Use up to 4 times daily or as directed by a doctor or dentist. Children 6 to under 12 years of age SUPERVISE USE

Children under 6 years of age:

- do not use

Other Infomation

store at 20-25°C (68-77°F)

Inactive Ingredients

anhydrous citric acid, cetylpyridinium chloride, dibasic sodium phosphate, edetate disodium, flavor, hydrochloric acid*, polyethylene glycol, propylene glycol, purified water, sodium hydroxide*, sucralose
*may contain this ingredient

Questions?

1-866-MUCINEX (1-866-682-4639)
You may also report side effects to this phone number.

Dist. by: RB Health (US)
Parsippany, NJ 07054-0224
©2023 RB Health
Made in Canada
www.mucinex.com

Keep out of reach of children.
In case of overdose, get medical help or contact a Poison Control Center right away.

Principle Display Panel

NDC: 72854-266-04

Mucinex® INSTASOOTHE™

Benzocaine 5.0mg oral pain reliever

Menthol 2.0mg oral pain reliever

✔ Numbs Pain Fast
✔ Maximum Cool

Product Label